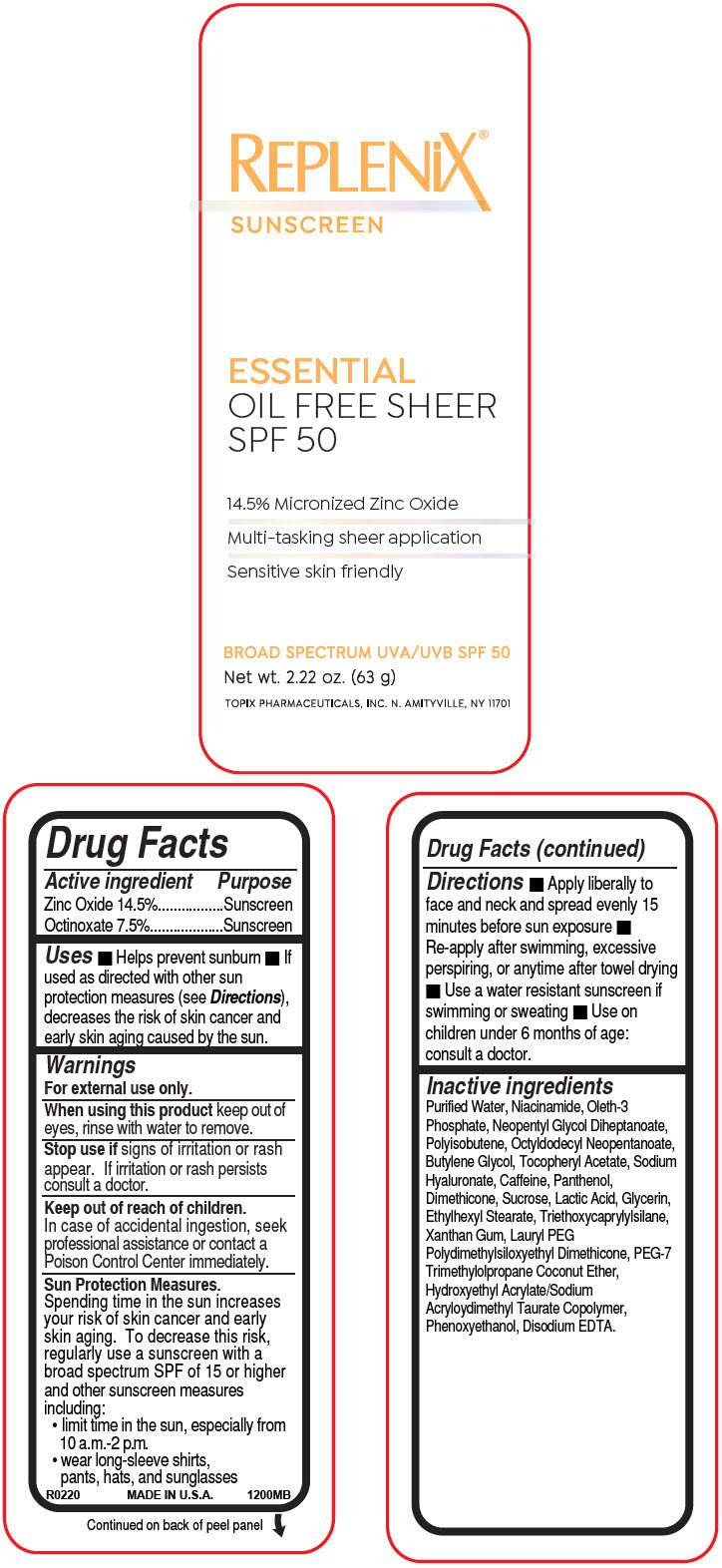 DRUG LABEL: Replenix  Sunscreen 
NDC: 51326-220 | Form: LOTION
Manufacturer: Topiderm, Inc.
Category: otc | Type: HUMAN OTC DRUG LABEL
Date: 20230224

ACTIVE INGREDIENTS: ZINC OXIDE 145 mg/1 g; OCTINOXATE 75 mg/1 g
INACTIVE INGREDIENTS: WATER; NIACINAMIDE; OLETH-3 PHOSPHATE; NEOPENTYL GLYCOL DIHEPTANOATE; OCTYLDODECYL NEOPENTANOATE; BUTYLENE GLYCOL; .ALPHA.-TOCOPHEROL ACETATE; HYALURONATE SODIUM; CAFFEINE; PANTHENOL; DIMETHICONE; SUCROSE; LACTIC ACID, DL-; GLYCERIN; ETHYLHEXYL STEARATE; TRIETHOXYCAPRYLYLSILANE; XANTHAN GUM; PEG-7 TRIMETHYLOLPROPANE COCONUT ETHER; PHENOXYETHANOL; EDETATE DISODIUM

Replenix® Sunscreen
SPF 50

Drug Facts

ACTIVE INGREDIENT

Active ingredient | Purpose
Zinc Oxide 14.5% | Sunscreen
Octinoxate 7.5% | Sunscreen

Uses

- Helps prevent sunburn
- If used as directed with other sun protection measures (see Directions), decreases the risk of skin cancer and early skin aging caused by the sun.

Warnings

For external use only.

When using this product keep out of eyes, rinse with water to remove.

Stop use if signs of irritation or rash appear. If irritation or rash persists consult a doctor.

Keep out of reach of children.

In case of accidental ingestion, seek professional assistance or contact a Poison Control Center immediately.

Sun Protection Measures

Spending time in the sun increases your risk of skin cancer and early skin aging. To decrease this risk, regularly use a sunscreen with a broad spectrum SPF of 15 or higher and other sunscreen measures including:

- limit time in the sun, especially from 10 a.m.-2 p.m.
- wear long-sleeve shirts, pants, hats, and sunglasses

Directions

- Apply liberally to face and neck and spread evenly 15 minutes before sun exposure
- Re-apply after swimming, excessive perspiring, or anytime after towel drying
- Use a water resistant sunscreen if swimming or sweating
- Use on children under 6 months of age: consult a doctor.

Inactive ingredients

Purified Water, Niacinamide, Oleth-3 Phosphate, Neopentyl Glycol Diheptanoate, Polyisobutene, Octyldodecyl Neopentanoate, Butylene Glycol, Tocopheryl Acetate, Sodium Hyaluronate, Caffeine, Panthenol, Dimethicone, Sucrose, Lactic Acid, Glycerin, Ethylhexyl Stearate, Triethoxycaprylylsilane, Xanthan Gum, Lauryl PEG Polydimethylsiloxyethyl Dimethicone, PEG-7 Trimethylolpropane Coconut Ether, Hydroxyethyl Acrylate/Sodium Acryloydimethyl Taurate Copolymer, Phenoxyethanol, Disodium EDTA.

PRINCIPAL DISPLAY PANEL - 63 g Bottle Label

REPLENiX®
SUNSCREEN

ESSENTIAL
OIL FREE SHEER
SPF 50

14.5% Micronized Zinc Oxide
Multi-tasking sheer application
Sensitive skin friendly

BROAD SPECTRUM UVA/UVB SPF 50

Net wt. 2.22 oz. (63 g)

TOPIX PHARMACEUTICALS, INC. N. AMITYVILLE, NY 11701